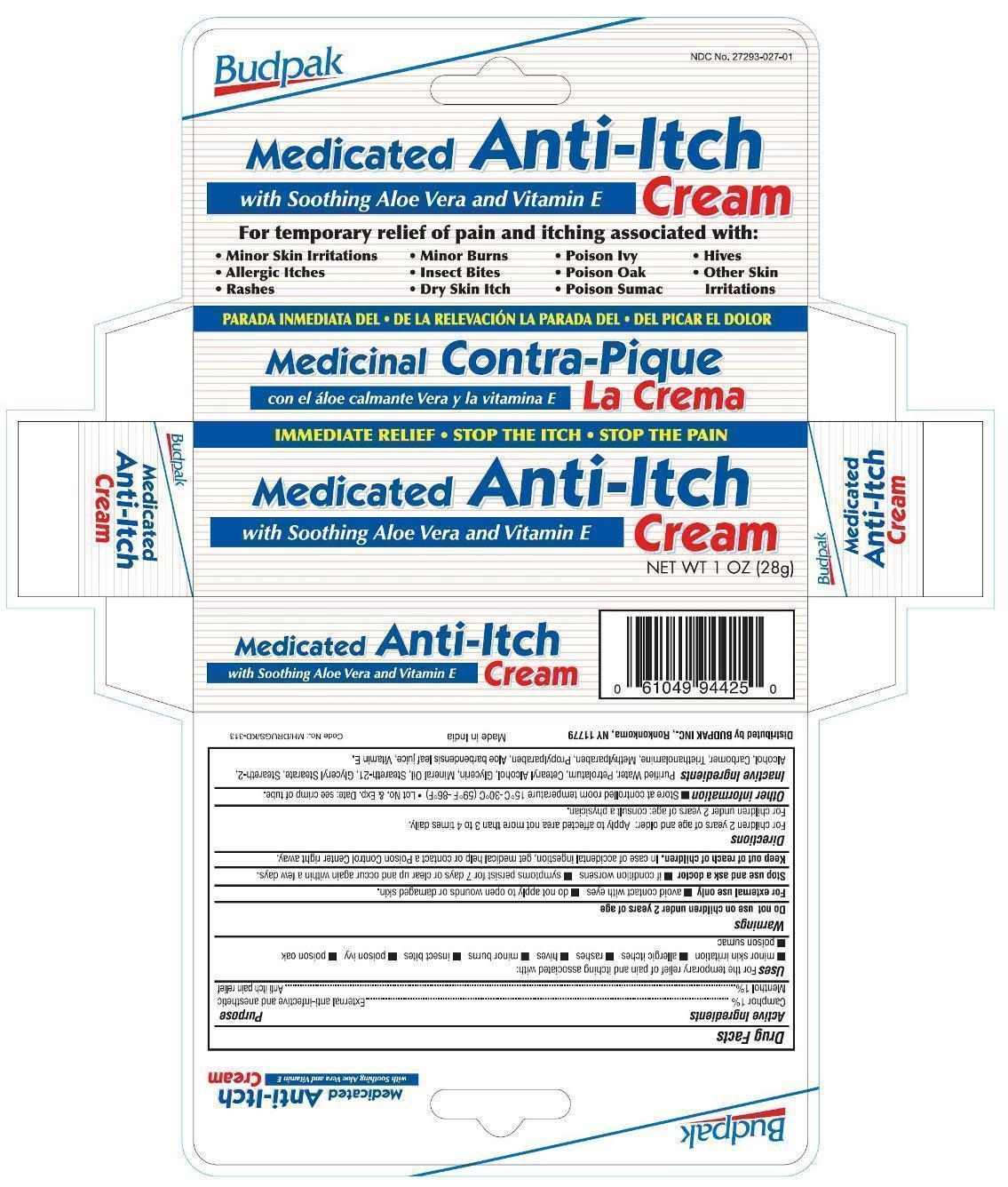 DRUG LABEL: Budpak Medicated Anti Itch
NDC: 27293-027 | Form: CREAM
Manufacturer: Budpak Inc. 
Category: otc | Type: HUMAN OTC DRUG LABEL
Date: 20130106

ACTIVE INGREDIENTS: CAMPHOR (SYNTHETIC) 0.01 g/1 g; MENTHOL 0.01 g/1 g
INACTIVE INGREDIENTS: WATER; PETROLATUM; CETOSTEARYL ALCOHOL; GLYCERIN; MINERAL OIL; STEARETH-21; GLYCERYL MONOSTEARATE; STEARETH-2; ALCOHOL; CARBOMER HOMOPOLYMER TYPE C (ALLYL PENTAERYTHRITOL CROSSLINKED); TROLAMINE; METHYLPARABEN; PROPYLPARABEN; ALOE VERA LEAF; .ALPHA.-TOCOPHEROL

Active Ingredients

Camphor 1%
Menthol 1%

Purpose

External anti-infective and anesthetic

Anti itch pain relief

Uses

For the temporary relief of pain and itching associated with:

- minor skin irritation
- allergic itches
- rashes
- hives
- minor burns
- insect bites
- poison ivy
- poison oak
- poison sumac

Warnings

For external use only

Do not use on children under 2 years of age.

- avoid contact with eyes
- do not apply to open wound or damaged skin.

Stop use and ask a doctor

- if condition worsens
- symptoms persist for 7 days or clear up and occur again within a few days.

Keep out of reach of children.

In case of accidental ingestion, get medical help or contact a Poison Control Center right away.

Directions

- For children 2 years of age and older: Apply to affected area not more than 3 to 4 times daily.
- For children under 2 years of age: consult a physician.

Other information

- Store at controlled room temperature 15ºC to 30ºC (59ºF to 86ºF)
- Lot No. & Exp. Date: see crimp of tube.

Inactive ingredients

Purified Water, Petrolatum, Cetearyl Alcohol, Glycerin, Mineral Oil, Steareth-21, Glyceryl Stearate, Steareth-2, Alcohol, Carbomer, Triethanolamine, Methylparaben, Propylparaben, Aloe barbadensis leaf juice, Vitamin E.

PRINCIPAL DISPLAY PANEL

Budpak Medicated Anti-Itch Cream

Camphor 1%

Menthol 1%

NET WT 1 OZ (28 g)